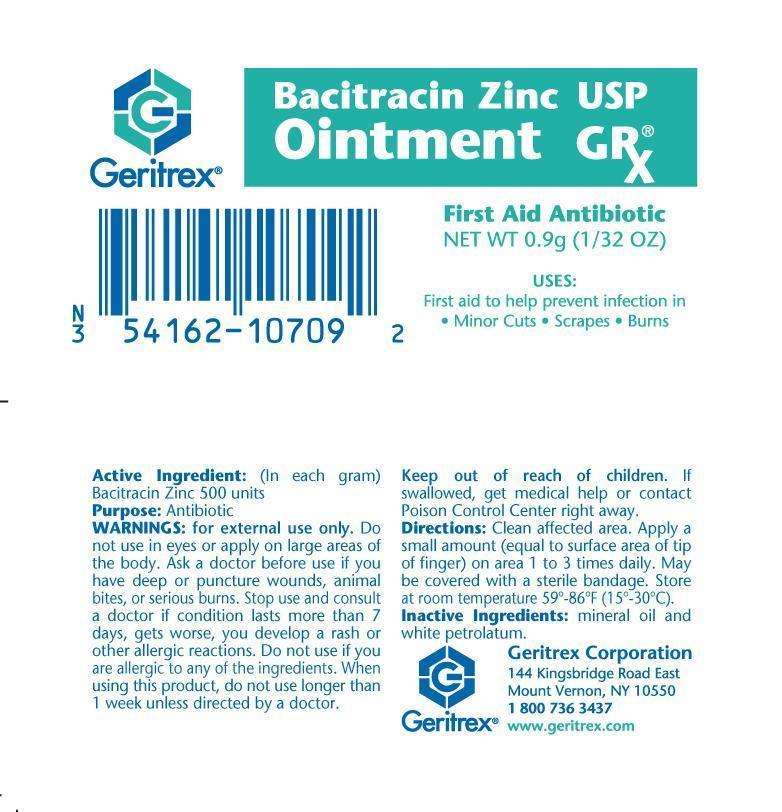 DRUG LABEL: Bacitracin Zinc
NDC: 54162-107 | Form: OINTMENT
Manufacturer: GERITREX CORP
Category: otc | Type: HUMAN OTC DRUG LABEL
Date: 20140723

ACTIVE INGREDIENTS: BACITRACIN ZINC 500 [iU]/1 g
INACTIVE INGREDIENTS: MINERAL OIL; PETROLATUM

Bacitracin Zinc Ointment